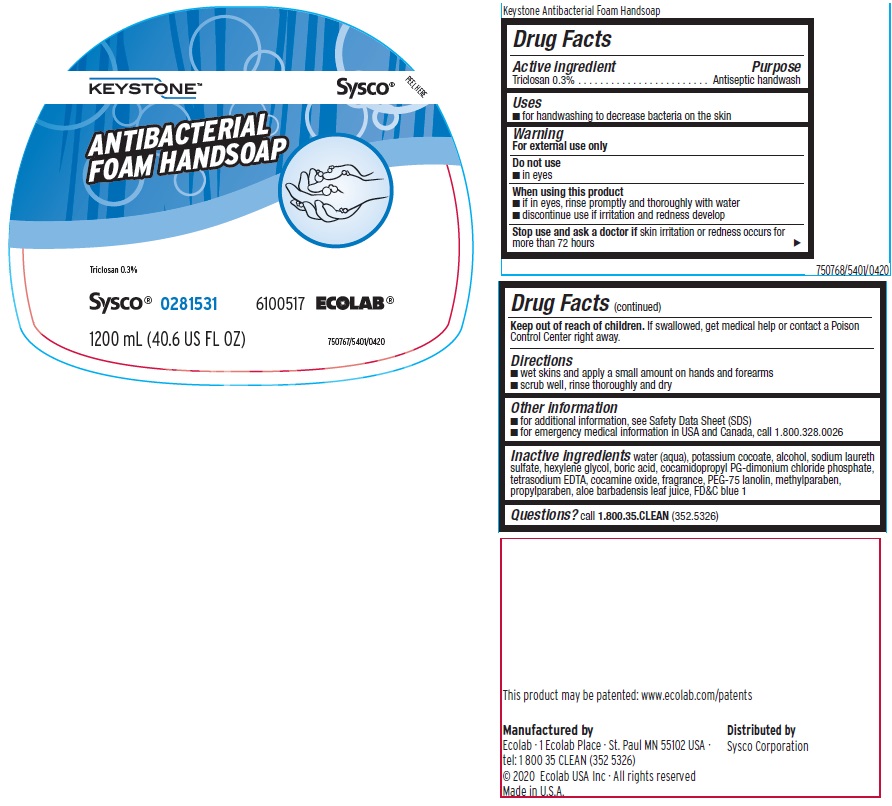 DRUG LABEL: Keystone
NDC: 47593-341 | Form: SOLUTION
Manufacturer: Ecolab Inc.
Category: otc | Type: HUMAN OTC DRUG LABEL
Date: 20240318

ACTIVE INGREDIENTS: TRICLOSAN 0.3 mg/100 mL
INACTIVE INGREDIENTS: WATER; POTASSIUM COCOATE; ALCOHOL; SODIUM LAURETH SULFATE; HEXYLENE GLYCOL; BORIC ACID; COCAMIDOPROPYL PG-DIMONIUM CHLORIDE PHOSPHATE; EDETATE SODIUM; COCAMINE OXIDE; PEG-75 LANOLIN; METHYLPARABEN; PROPYLPARABEN; ALOE VERA LEAF; FD&C BLUE NO. 1

Drug Facts

Active ingredient

Triclosan 0.3%

Purpose

Antiseptic handwash

Uses

- for handwashing to decrease bacteria on the skin

Warnings

For external use only

Do not use

- in eyes

When using this product

- if in eyes, rinse promptly and thoroughly with water
- discontinue use if irritation and redness develop

Stop use and ask a doctor if

- skin irritation or redness occurs for more than 72 hours

Keep out of reach of children. If swallowed, get medical help or contact a Poison Control Center right away.

Directions

- wet skins and apply a small amount on hands an forearms
- scrub well, rinse thoroughly and dry

Other information

- for additional information see, Safety Data Sheet (SDS)
- for emergency medical information in USA and Canada, call 1.800.328.0026

INACTIVE INGREDIENT

Inactive ingredients water (aqua), potassium cocoate, alcohol, sodium laureth sulfate, hexylene glycol, boric acid, cocamidopropyl PG-dimonium chloride phosphate, tetrasodium EDTA, cocamine oxide, fragrance, PEG-75 lanolin, methylparaben, propylparaben, aloe barbadensis leaf juice, FD&C blue 1

Questions? call 1.800.35.CLEAN (352.5326)

Principal display panel and representative label

KEYSTONE

ANTIBACTERIAL FOAM HANDSOAP

Triclosan 0.3%

SYSCO 0281531

6100517 ECOLAB

Net Contents: 1200 mL (40.6 US fl oz)

750767/5401/0420

Distributed by

Sysco Corporation

Manufactured by

Ecolab · 1 Ecolab Place · St. Paul MN 55102 USA ·

tel: 1 800 35 CLEAN (352 5326)

© 2020 Ecolab USA Inc · All rights reserved

Made in U.S.A.